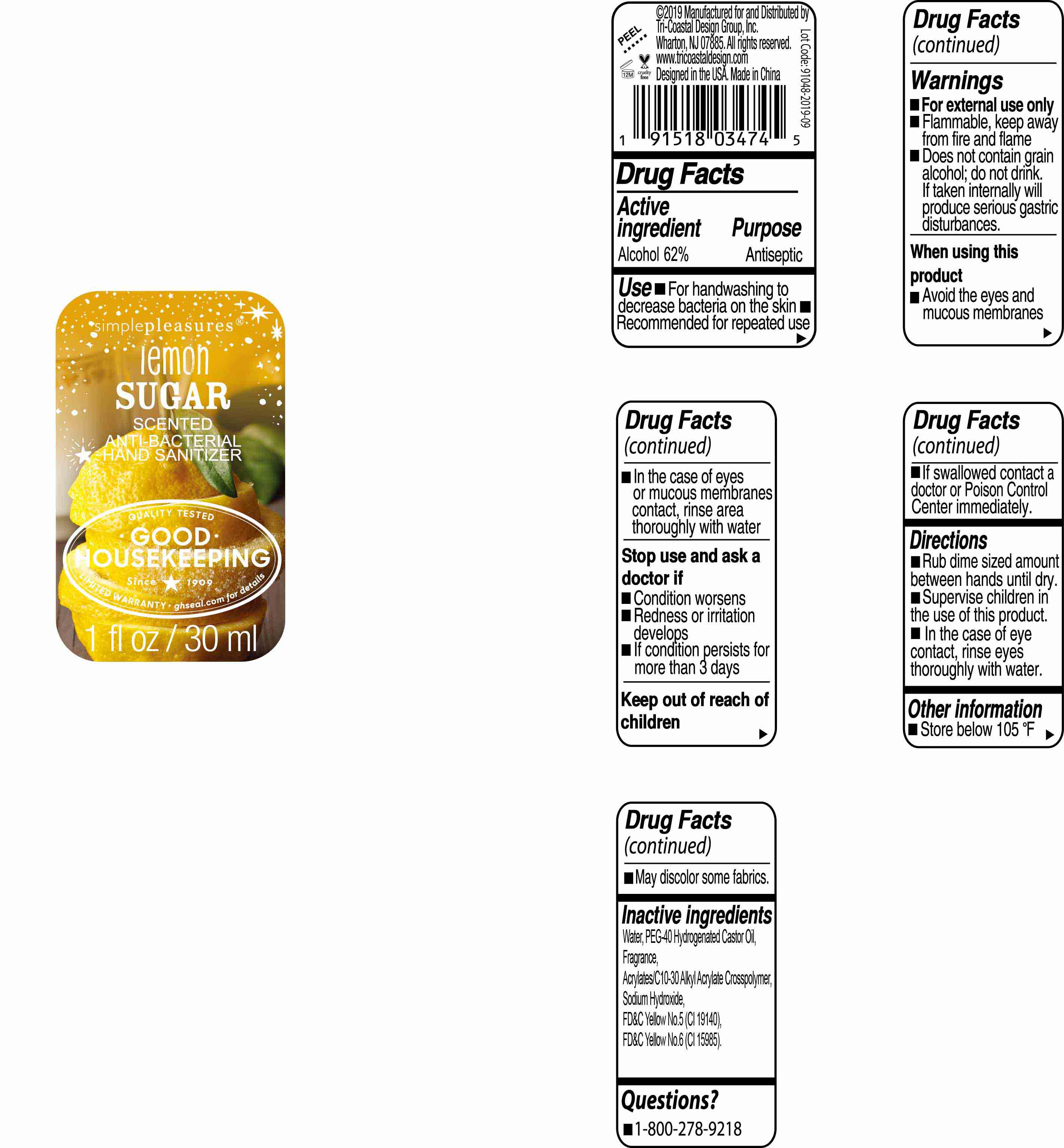 DRUG LABEL: simplepleasures
NDC: 49852-159 | Form: LIQUID
Manufacturer: Tri-Coastal Design Company Inc.
Category: otc | Type: HUMAN OTC DRUG LABEL
Date: 20200701

ACTIVE INGREDIENTS: ALCOHOL 62 g/100 mL
INACTIVE INGREDIENTS: FD&C YELLOW NO. 6; FD&C YELLOW NO. 5; WATER; CARBOMER INTERPOLYMER TYPE A (55000 CPS); POLYOXYL 40 HYDROGENATED CASTOR OIL; SODIUM HYDROXIDE

simplepleasures lemon sugar Hand Sanitizer

Active Ingredient

Alcohol 62%

Purpose

Antiseptic

Uses

■ For handwashing to decrease bacteria on the skin

■ Recommended for repeated use

Warnings

■ For external use only ■ Flammable, keep away from fire and flame ■ Does not contain grain alcohol; do not drink, if taken internally will produce serious gastric disturbances

When using this product

■ Avoid the eyes and mucous membranes ■ In the case of eyes or mucous membrane contact; rinse area thoroughly with water

Stop use and ask a doctor if

■ Condition worsens ■ Redness or irritation develops ■ If condition persists for more than 3 days

Keep out of reach of children

■ If swallowed, get medical help or Poison Control Center right away.

Directions

■ Rub dime sized amount between hands until dry ■ Supervise children in the use of this product ■ In the case of eye contact, rinse eyes thoroughly with water.

Other information

■ Store below 105ºF ■ May discolor some fabrics

Inactive ingredients

Water, PEG-40 Hydrogenated Castor Oil, Fragrance, Acrylates/C10-30 Alkyl Acetate Crosspolymer, Sodium Hydroxide, FD&C Yellow No. 5 (CI 19140), FD&C Yellow No. 6 (CI 15985)

Questions?

■ 1-800-278-9218